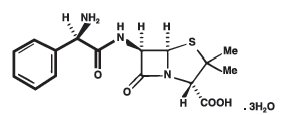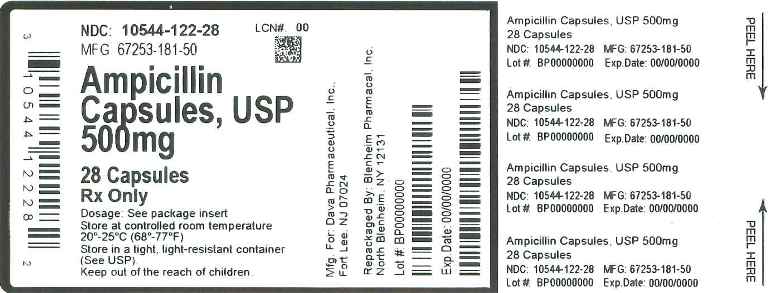 DRUG LABEL: Ampicillin
NDC: 10544-122 | Form: CAPSULE
Manufacturer: Blenheim Pharmacal, Inc.
Category: prescription | Type: HUMAN PRESCRIPTION DRUG LABEL
Date: 20150316

ACTIVE INGREDIENTS: AMPICILLIN TRIHYDRATE 500 mg/1 1
INACTIVE INGREDIENTS: MAGNESIUM STEARATE; FERROSOFERRIC OXIDE; GELATIN; SILICON DIOXIDE; SODIUM LAURYL SULFATE; TITANIUM DIOXIDE; D&C RED NO. 28; FD&C BLUE NO. 1

AMPICILLIN CAPSULES, USP 250 mg and 500 mg
AMPICILLIN FOR ORAL SUSPENSION, USP 125 mg/5 mL and 250 mg/5 mL
Rx Only

To reduce the development of drug-resistant bacteria and maintain the effectiveness of Ampicillin capsules, Ampicillin for Oral Suspension and other antibacterial drugs, Ampicillin Capsules and Ampicillin for Oral Suspension should be used only to treat or prevent infections that are proven or strongly suspected to be caused by bacteria.

CLINICAL PHARMACOLOGY

Ampicillin is bactericidal at low concentrations and is clinically effective not only against the gram-positive organisms usually susceptible to penicillin G but also against a variety of gram-negative organisms. It is stable in the presence of gastric acid and is well absorbed from the gastrointestinal tract. It diffuses readily into most body tissues and fluids; however, penetration into the cerebrospinal fluid and brain occurs only with meningeal inflammation. Ampicillin is excreted largely unchanged in the urine; its excretion can be delayed by concurrent administration of probenecid which inhibits the renal tubular secretion of ampicillin. In blood serum, ampicillin is the least bound of all the penicillins; an average of about 20 percent of the drug is bound to the plasma proteins as compared to 60 to 90 percent of the other penicillins. The administration of 500 mg dose of ampicillin trihydrate capsules results in an average peak blood serum level of approximately 3.0 mcg/mL; the average peak serum level for a 250 mg dose of ampicillin trihydrate for oral suspension is approximately 2.3 mcg/mL.

Microbiology: While in vitro studies have demonstrated the susceptibility of most strains of the following organisms, clinical efficacy for infections other than those included in the INDICATIONS AND USAGE section has not been documented.

GRAM-POSITIVE - strains of alpha- and beta-hemolytic streptococci, Streptococcus pneumoniae, those strains of staphylococci, which do not produce penicillinase, Clostridium sp., Bacillus anthracis, Corynebacterium xerose, and most strains of enteracocci.

GRAM-NEGATIVE – Hemophilus influenzae; Neisseria gonorrhoeae and N. Meningitidis, Proteus mirabilis and many strains of Salmonella (including S. typhosa), Shigella and Escherichia coli.

NOTE: Ampicillin is inactivated by penicillinase and therefore is ineffective against penicillinase-producing organisms including certain strains at staphylococci, Pseudomonas aeruginosa, P. vulgaris, Klebsiella pneumoniae, Enterobacter aerogenes, and some strains of E. coli. Ampicillin is not active against Rickettsia, Mycoplasma, and "large viruses" (Miyagawanella).

TESTING FOR SUSCEPTIBILITY: The invading organism should be cultured and its susceptibility demonstrated as a guide to therapy. If the Kirby-Bauer method of disc susceptibility is used, a 10 mcg ampicillin disc should be used to determine the relative in vitro susceptibility.

INDICATIONS AND USAGE

To reduce the development of drug-resistant bacteria and maintain the effectiveness of Ampicillin capsules, Ampicillin for Oral Suspension and other antibacterial drugs, Ampicillin capsules and Ampicillin for Oral Suspension should be used only to treat or prevent infections that are proven or strongly suspected to be caused by bacteria. When culture and susceptibility information are available, they should be considered in selecting of modifying anitimicrobial therapy, in the absence of such data, local epidemiology and susceptibility patterns contribute to the empiric selection of therapy.

Ampicillin capsules and Ampicillin for oral suspension are indicated in the treatment of infections caused by susceptible strains of the designated organisms listed below:

Infections of the genitourinary tract including gonorrhea - E. coli, P. mirabilis, enterococci, Shigella, S. typhosa and other Salmonella and nonpenicillinase-producing N. gonorrhoeae.

Infections of the respiratory tract - Nonpenicillinase-producing H. influenzae and staphylococci, and streptococci including Streptococcus pneumoniae.

Infections of the gastrointestinal tract - Shigella, S. typhosa and other Salmonella, E. coli, P. mirabilis, and enterococci.

Meningitis - N. Meningitidis

Bacteriology studies to determine the causative organisms and their susceptibility to ampicillin should be performed. Therapy may be instituted prior to the results of susceptibility testing.

CONTRAINDICATIONS

A history of a previous hypersensitivity reaction to any of the penicillins is a contraindication. Ampicillin is also contraindicated in infections caused by penicillinase-producing organisms.

WARNINGS

SERIOUS AND OCCASIONALLY FATAL HYPERSENSITIVITY (ANAPHYLACTOID) REACTIONS HAVE BEEN REPORTED IN PATIENTS ON PENICILLIN THERAPY. ALTHOUGH ANAPHYLAXIS IS MORE FREQUENT FOLLOWING PARENTERAL THERAPY, IT HAS OCCURRED IN PATIENTS ON ORAL PENICILLINS. THESE REACTIONS ARE MORE LIKELY TO OCCUR IN INDIVIDUALS WITH A HISTORY OF SENSITIVITY TO MULTIPLE ALLERGENS. THERE HAVE BEEN REPORTS OF INDIVIDUALS WITH A HISTORY OF PENICILLIN HYPERSENSITIVITY WHO HAVE EXPERIENCED SEVERE REACTIONS WHEN TREATED WITH CEPHALOSPORINS. BEFORE THERAPY WITH ANY PENICILLIN, CAREFUL INQUIRY SHOULD BE MADE CONCERNING PREVIOUS HYPERSENSITIVITY REACTIONS TO PENICILLINS, CEPHALOSPORINS, OR OTHER ALLERGENS. IF AN ALLERGIC REACTION OCCURS, APPROPRIATE THERAPY SHOULD BE CONSIDERED. SERIOUS ANAPHYLACTOID REACTIONS REQUIRE IMMEDIATE EMERGENCY TREATMENT WITH EPINEPHRINE. OXYGEN, INTRAVENOUS STEROIDS, AND AIRWAY MANAGEMENT, INCLUDING INTUBATION, SHOULD ALSO BE ADMINISTERED AS INDICATED.

Pseudomembranous colitis has been reported with nearly all antibacterial agents, including ampicillin, and may range in severity from mild to life-threatening. Therefore, it is important to consider this diagnosis in patients who present with diarrhea subsequent to the administration of antibacterial agents.

Treatment with antibacterial agents alters the normal flora of the colon and may permit overgrowth of clostridia. Studies indicate that a toxin produced by Clostridium difficile is a primary cause of "antibiotic-associated colitis".

After the diagnosis of pseudomembranous colitis has been established, therapeutic measures should be initiated. Mild cases of pseudomembranous colitis usually respond to discontinuation of the drug alone. In moderate to severe cases, consideration should be given to management with fluids and electrolytes, protein supplementation, and treatment with an antibacterial drug clinically effective against C. difficile colitis.

PRECAUTIONS

General

Prescribing Ampicillin capsules and Ampicillin for Oral Suspension in the absence of a proven or strongly suspected bacterial infection of a prophylactic indication is unlikely to provide benefit to the patient and increases the risk of the development of drug-resistant bacteria.

Prolonged use of antibiotics may promote the overgrowth of nonsusceptible organisms, including fungi.
Should superinfection occur, appropriate measures should be taken.
Patients with gonorrhea who also have syphilis should be given additional appropriate parenteral penicillin treatment.
Treatment with ampicillin does not preclude the need for surgical procedures, particularly in staphylococcal infections.

Information for the patient

1. The patient should inform the physician of any history of sensitivity to allergens, including previous hypersensitivity reactions to penicillins and cephalosporins (see WARNINGS).
2. The patient should discontinue ampicillin and contact the physician immediately if any side effect occurs (see WARNINGS).
3. Ampicillin should be taken with a full glass (8 oz) of water, one-half hour before or two hours after meals.
4. Diabetic patients should consult with the physician before changing diet or dosage of diabetes medication (see PRECAUTIONS, Drug/Laboratory Test Interactions).

Patients should be counseled that antibacterial drugs, including Ampicillin capsules and Ampicillin for Oral Suspension should only be used to treat bacterial infections. They do not treat viral infections (e.g. the common cold).

When Ampicilin capsules or Ampicillin for Oral Suspension are prescribed to treat a bacterial infection, patients should be told that, although it is common to feel better early in the course of therapy, the medication should be taken exactly as directed. Skipping doses or not completing the full course of therapy may:

(i) Decrease the effectiveness of the immediate treatment, and

(ii) Increase the likelihood that bacteria will develop resistance and will not be treatable by Ampicillin capsules and Ampicillin for Oral Suspension or other antibacterial drugs in the future

Laboratory Tests

In prolonged therapy, and particularly with high dosage regimens, periodic evaluation of the renal, hepatic and hematopoietic systems is recommended. In streptococcal infections, therapy must be sufficient to eliminate the organism (10 days minimum); otherwise the sequelae of streptococcal disease may occur. Cultures should be taken following completion of treatment to determine whether streptococci have been eradicated. Cases of gonococcal infection with a suspected lesion of syphilis should have darkfield examinations ruling out syphilis before receiving ampicillin. Patients who do not have suspected lesions of syphilis and are treated with ampicillin should have a follow-up serologic test for syphilis each month for four months to detect syphilis that may have been masked from treatment for gonorrhea.

Drug Interactions

When administered concurrently, the following drugs may interact with ampicillin:

Allopurinol - Increased possibility of skin rash; particularly in hyperuricemic patients may occur.

Bacteriostatic antibiotics - Chloramphenicol, erythromycins, sulfonamides, or tetracyclines may interfere with the bactericidal effect of penicillins. This has been demonstrated in vitro; however, the clinical significance of this interaction is not well-documented.

Oral contraceptives - May be less effective and increased breakthrough bleeding may occur.

Probenecid - May decrease renal tubular secretion of ampicillin resulting in increased blood levels and/or ampicillin toxicity.

Drug/Laboratory Test Interactions

After treatment with ampicillin, a false-positive reaction for glucose in the urine may occur with copper sulfate tests (Benedict's solution, Fehling's solution, or Clinitest® tablets) but not with enzyme based tests such as Clinistix® and Tes-Tape® (Glucose Enzymatic Test Strip USP).

Carcinogenesis, Mutagenesis, Impairment of Fertility

Long-term studies in animals have not been performed to evaluate carcinogenesis, mutagenesis, or impairment of fertility in males or females.

Pregnancy

Teratogenic Effects

Category B:

Reproduction studies in animals have revealed no evidence of impaired fertility or harm to the fetus due to penicillin. There are, however, no adequate and well-controlled studies in pregnant women. Because animal reproduction studies are not always predictive of human response, penicillin should be used during pregnancy only if clearly needed.

Labor and Delivery

Oral ampicillin-class antibiotics are poorly absorbed during labor. Studies in guinea pigs showed that intravenous administration of ampicillin slightly decreased the uterine tone and frequency of contractions, but moderately increased the height and duration of contractions. However, it is not known whether use of these drugs in humans during labor or delivery has immediate or delayed adverse effects on the fetus, prolongs the duration of labor, or increases the likelihood that forceps delivery or other obstetrical intervention or resuscitation of the newborn will be necessary.

Nursing Mothers

Ampicillin-class antibiotics are excreted in milk. Ampicillin used by nursing mothers may lead to sensitization of infants; therefore, a decision should be made whether to discontinue nursing or to discontinue ampicillin, taking into account the importance of the drug to the mother.

Pediatric Use

Penicillins are excreted primarily unchanged by the kidney; therefore, the incompletely developed renal function in neonates and young infants will delay the excretion of penicillin. Administration to neonates and young infants should be limited to the lowest dosage compatible with an effective therapeutic regime (see DOSAGE AND ADMINISTRATION).

ADVERSE REACTIONS

As with other penicillins, it may be expected that untoward reactions will be essentially limited to sensitivity phenomena. They are more likely to occur in individuals who have previously demonstrated hypersensitivity to penicillin and in those with a history of allergy, asthma, hay fever or urticaria.

The following adverse reactions have been reported as associated with the use of ampicillin:

Gastrointestinal: glossitis, stomatitis, nausea, vomiting, enterocolitis, pseudomembranous colitis, and diarrhea. These reactions are usually associated with oral dosage forms of the drug.

Hypersensitivity Reactions: An erythematous, mildly pruritic, maculopapular skin rash has been reported fairly frequently. The rash, which usually does not develop within the first week of therapy, may cover the entire body including the soles, palms, and oral mucosa. The eruption usually disappears in three to seven days. Other hypersensitivity reactions that have been reported are: skin rash, pruritus, urticaria, erythema multiforme, and an occasional case of exfoliative dermatitis. Anaphylaxis is the most serious reaction experienced and has usually been associated with the parenteral dosage form of the drug.

NOTE: Urticaria, other skin rashes, and serum sickness-like reactions may be controlled by antihistamines, and, if necessary, systemic corticosteroids. Whenever such reactions occur, ampicillin should be discontinued unless, in the opinion of the physician, the condition being treated is life-threatening and amenable only to ampicillin therapy. Serious anaphylactoid reactions require emergency measures (see WARNINGS).

Liver: Moderate elevation in serum glutamic oxaloacetic transaminase (SGOT) has been noted, but the significance of this finding is unknown.

Hemic and Lymphatic Systems: anemia, thrombocytopenia, thrombocytopenic purpura, eosinophilia, leukopenia, and agranulacytosis have been reported during therapy with penicillins. These reactions are usually reversible on discontinuation of therapy and are believed to be hypersensitivity phenomena.

Other adverse reactions that have been reported with the use of ampicillin are laryngeal stridor and high fever. An occasional patient may complain of sore mouth or tongue as with any oral penicillin preparation.

OVERDOSAGE

In case of overdosage, discontinue medication, treat symptomatically and institute supportive measures as required. In patients with renal function impairment, ampicillin-class antibiotics can be removed by hemodialysis but not by peritoneal dialysis.

DOSAGE AND ADMINISTRATION

Adults and children weighing over 20 Kg: For genitourinary or gastrointestinal tract infections other than gonorrhea in men and women, the usual dose is 500 mg q.i.d. in equally spaced doses; severe or chronic infections may require larger doses. For the treatment of gonorrhea in both men and women, a single oral dose of 3.5 grams of ampicillin administered simultaneously with 1 gram of probenecid is recommended. Physicians are cautioned to use no less than the above recommended dosage for the treatment of gonorrhea. Follow-up cultures should be obtained from the original site(s) of infection 7 to 14 days after therapy. In women, it is also desirable to obtain culture test-of-cure from both the endocervical and anal canals. Prolonged intensive therapy is needed for complications such as prostatitis and epididymitis. For respiratory tract infections, the usual dose is 250 mg q.i.d. in equally spaced doses.

Pediatric Patients weighing 20 Kg or less: For genitourinary or gastrointestinal tract infections, the usual dose is 100 mg/kg/day total, q.i.d. in equally divided and spaced doses.

For respiratory tract infections, the usual dose is 50 mg/kg/day total, in equally divided and spaced doses three to four times daily. Doses for children should not exceed doses recommended for adults.

All patients, irrespective of age and weight: Larger doses may be required for severe or chronic infections. Although ampicillin is resistant to degradation by gastric acid, it should be administered at least one half-hour before or two hours after meals for maximal absorption. Except for the single dose regimen for gonorrhea referred to above, therapy should be continued for a minimum of 48 to 72 hours after the patient becomes asymptomatic or evidence at bacterial eradication has been obtained. In infections caused by haemolytic strains of streptococci, a minimum of 10 days' treatment is recommended to guard against the risk of rheumatic fever or glomerulonephritis (see PRECAUTIONS, Laboratory Tests). In the treatment of chronic urinary or gastrointestinal infections, frequent bacteriologic and clinical appraisal is necessary during therapy and may be necessary for several months afterwards. Stubborn infections may require treatment for several weeks. Smaller doses than those indicated above should not be used.

Directions for mixing Oral Suspension

Prepare suspension at time of dispensing. For ease of preparation, add water to the bottle in two portions and shake well after each addition.

125 mg/5 mL
Add a total of 86 mL to the 100 mL package and 170 mL to the 200 mL package. This will provide 100 mL and 200 mL of suspension. Each 5 mL (teaspoonful) will contain ampicillin trihydrate equivalent to 125 mg ampicillin.

250 mg/5 mL
Add a total of 70 mL to the 100 mL package and 139 mL to the 200 mL package. This will provide 100 mL and 200 mL of suspension . Each 5 mL (teaspoonful) will contain ampicillin trihydrate equivalent to 250 mg ampicillin.

HOW SUPPLIED

Ampicillin Capsules, USP 250 mg: Each capsule contains ampicillin trihydrate equivalent to 250 mg ampicillin. The number 2 size capsule has a gray opaque body with a light blue opaque cap, printed WC402.

Bottles of 100 NDC 67253-180-10
Bottles of 500 NDC 67253-180-50

Ampicillin Capsules, USP 500 mg: Each capsule contains ampicillin trihydrate equivalent to 500 mg ampicillin. The number 0 size capsule has a gray opaque body with a light blue opaque cap, printed WC404.

Bottles of 100 NDC 67253-181-10
Bottles of 500 NDC 67253-181-50

Store at 20° to 25°C (68° to 77°F) [See USP Controlled Room Temperature].

Ampicillin for Oral Suspension, USP is available as a powder which when reconstituted as directed yields a white, bubble gum flavoured suspension.

Ampicillin for Oral Suspension, USP 125 mg/5 mL: Each 5 mL of reconstituted suspension contains ampicillin trihydrate equivalent to 125 mg ampicillin.

100 mL bottles NDC 67253-182-10
200 mL bottles NDC 67253-182-20

Ampicillin for Oral Suspension, USP 250 mg/5 mL: Each 5 mL of reconstituted suspension contains ampicillin trihydrate equivalent to 250 mg ampicillin.

100 mL bottles NDC 67253-183-10
200 mL bottles NDC 67253-183-20

Store dry powder at 20° to 25°C (68° to 77°F) [See USP Controlled Room Temperature].

Store the reconstituted suspension in a refrigerator. Discard any unused portion after 14 days.

Manufactured for: DAVA Pharmaceuticals, Inc.
Fort Lee, NJ 07024, USA

by: STADA Production Ireland Ltd.
Clonmel, Ireland.

Rev. 01/11

181G451

DESCRIPTION

Ampicillin trihydrate is a semisynthetic penicillin derived from the basic penicillin nucleus, 6-aminopenicillanic acid. Ampicillin is designated chemically as (2S, 5R, 6R)-6-[(R)-2-Amino-2-phenylacetamido]-3, 3-dimethyl-7-oxo-4-thia-l-azabicyclo[3.2.0]heptane-2-carboxylic acid trihydrate.

It has the following chemical structure:

The molecular formula is C16H19N3O4S.3H2O, and the molecular weight is 403.45.

Ampicillin Capsules, USP for oral administration provide ampicillin trihydrate equivalent to 250 mg and 500 mg ampicillin. Ampicillin Capsules, USP also contains magnesium stearate, NF. The capsule shell contains black iron oxide; D&C red No. 28; FD&C blue No. 1; gelatin, NF; silicon dioxide, NF; sodium lauryl sulfate, NF; titanium dioxide USP.

Ampicillin for Oral Suspension, USP provides ampicillin trihydrate equivalent to 125 mg/5 mL and 250 mg/5 mL ampicillin. Ampicillin for Oral Suspension, USP also contains flavors; microcrystalline cellulose and carboxymethylcellulose sodium, NF; colloidal silicon dioxide, NF; sodium citrate, USP; sodium propionate, NF; sucrose, NF

Principal Display Panel

Ampicillin Capsules, USP 500mg

28 Capsules

NDC 10544-122-28